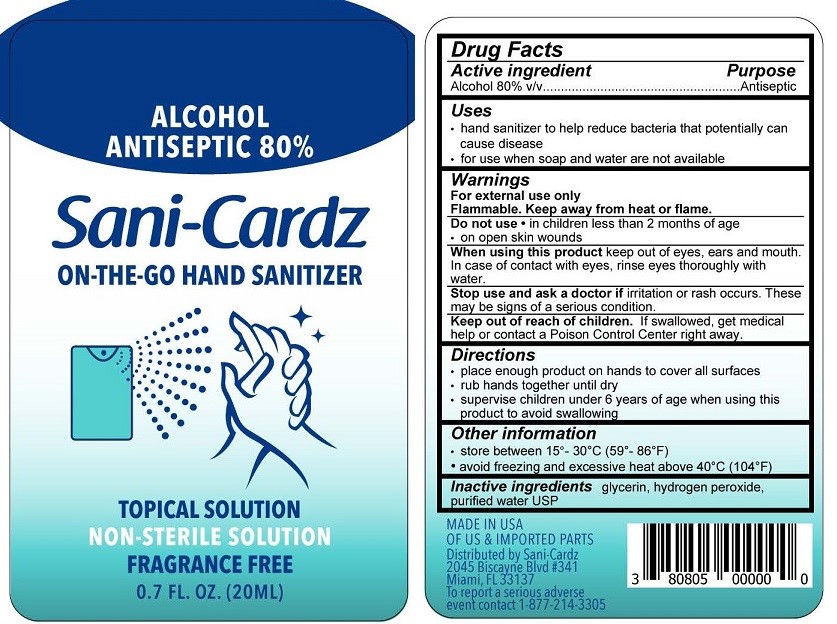 DRUG LABEL: Sani-Cardz
NDC: 80805-001 | Form: SOLUTION
Manufacturer: TVG Products, LLC
Category: otc | Type: HUMAN OTC DRUG LABEL
Date: 20201030

ACTIVE INGREDIENTS: ALCOHOL 80 mL/100 mL
INACTIVE INGREDIENTS: HYDROGEN PEROXIDE; GLYCERIN; WATER

Sani-Cardz Hand Sanitizer

Drug Facts

Active ingredient

Alcohol 80% v/v

Purpose

Antiseptic

Uses

- hand sanitizer to help reduce bacteria that potentially can cause disease
- for use when soap and water are not available

Warnings
For external use only.

Flammable. Keep away from heat or flame.

Do not use

- in children less than 2 months of age
- on open skin wounds

When using this product keep out of eyes, ears, and mouth. In case of contact with eyes, rinse eyes thoroughly with water.

Stop use and ask a doctor if irritation or rash occurs. These may be signs of a serious condition.

Keep out of reach of children. If swallowed, get medical help or contact a Poison Control Center right away.

Directions

- place enough product on hands to cover all surfaces
- rub hands together until dry
- supervise children under 6 years of age when using this product to avoid swallowing

Other information

- store between 15°-30°C (59°-86°F)
- avoid freezing and excessive heat above 40°C (104°F)

Inactive ingredients glycerin, hydrogen peroxide, purified water USP

MADE IN USA OF US & IMPORTED INGREDIENTS

Distributed by Sani-Cardz

2045 Biscayne Blvd #341

Miami, FL 33137

To report a serious adverse event contact 1-877-214-3305

PACKAGE LABEL

ALCOHOL ANTISEPTIC 80%
Sani-Cardz
ON-THE-GO HAND SANITIZER
TOPICAL SOLUTION
NON-STERILE SOLUTION
0.7 FL. OZ. (20ML)